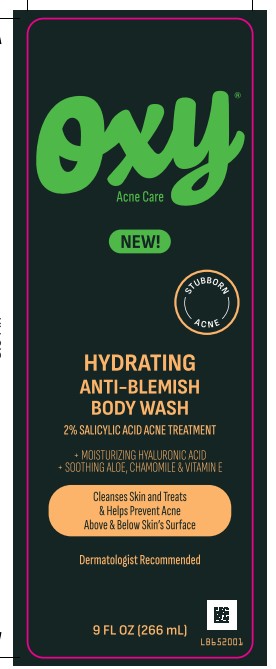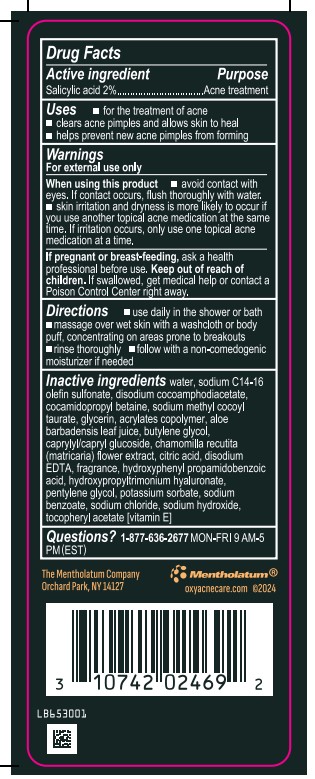 DRUG LABEL: Oxy Hydrating Anti-Blemish Body Wash
NDC: 10742-1009 | Form: GEL
Manufacturer: The Mentholatum Company
Category: otc | Type: HUMAN OTC DRUG LABEL
Date: 20241123

ACTIVE INGREDIENTS: SALICYLIC ACID 18 mg/1 mL
INACTIVE INGREDIENTS: ALPHA-TOCOPHEROL ACETATE; COCAMIDOPROPYL BETAINE; HYALURONIC ACID; EDETATE DISODIUM; HYDROXYPHENYL PROPAMIDOBENZOIC ACID; PENTYLENE GLYCOL; GLYCERIN; SODIUM BENZOATE; SODIUM HYDROXIDE; ACRYLIC ACID/SODIUM ACRYLATE COPOLYMER (1:1; 600 MPA.S AT 0.2%); CAPRYLYL/CAPRYL OLIGOGLUCOSIDE; CHAMOMILE; SODIUM C14-16 OLEFIN SULFONATE; DISODIUM COCOAMPHODIACETATE; SODIUM CHLORIDE; WATER; SODIUM METHYL COCOYL TAURATE; POTASSIUM SORBATE; ALOE VERA LEAF; BUTYLENE GLYCOL; ANHYDROUS CITRIC ACID; FRAGRANCE 13576

Drug Facts

Active ingredient

Salicylic acid 2%

Purpose

Acne treatment

Uses

- for the treatment of acne
- clears acne pimples and allows skin to heal
- helps prevent new acne pimples from forming

WARNINGS

For external use only

When using this product

- avoid contact with eyes. If contact occurs, flush thoroughly with water.
- skin irritation and dryness is more likely to occur if you use another topical acne medication at the same time. If irritation occurs, only use one topical acne medication at a time.

If pregnant or breast-feeding,

ask a health professional before use.

Directions

- use daily in the shower or bath
- massage over wet skin with a washcloth or body puff, concentrating on areas prone to breakouts
- rinse thoroughly
- follow with a non-comedogenic moisturizer if needed

Inactive ingredients

water, sodium C14-16 olefin sulfonate, disodium cocoamphodiacetate, cocamidopropyl betaine, sodium methyl cocoyl taurate, glycerin, acrylates copolymer, aloe barbadensis leaf juice, butylene glycol, caprylyl/capryl glucoside, chamomilla recutita (matricaria) flower extract, citric acid, disodium EDTA, fragrance, hydroxyphenyl propamidobenzoic acid, hydroxypropyltrimonium hyaluronate, pentylene glycol, potassium sorbate, sodium benzoate, sodium chloride, sodium hydroxide, tocopheryl acetate [vitamin E]

Questions

1-877-636-2677 MON-FRI 9 AM to 5 PM (EST)

Keep out of reach of children

If swallowed, get medical help or contact a Poison Control Center right away.